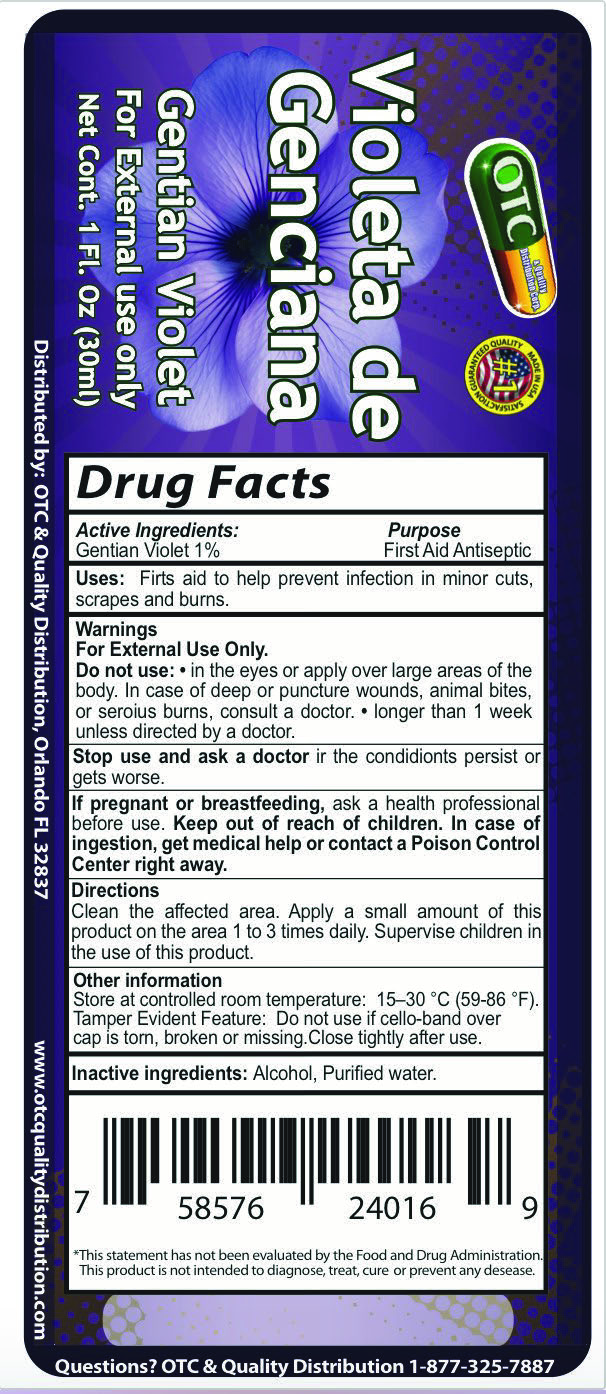 DRUG LABEL: Gentian Violet
NDC: 69469-010 | Form: SOLUTION
Manufacturer: Vitamex USA, Corp
Category: otc | Type: HUMAN OTC DRUG LABEL
Date: 20240906

ACTIVE INGREDIENTS: GENTIAN VIOLET 10 mg/1 mL
INACTIVE INGREDIENTS: WATER; ALCOHOL

Gentian Violet 1oz

Active Ingredients:

Active Ingredients: Purpose

Gentian Violet 1% First Aid Antiseptic

Uses:

Uses: First aid to help prevent infection in minor cuts, scrapes and burns.

Warnings:

For External Use Only

Do not use in the eyes or apply over large areas of the body. In case of deep or puncture wounds, animal bites, or serious burns, consult a doctor, longer than 1 week unless directed by a doctor.

Stop use and ask a doctor: if the the conditions presist or get worse.

If pregnant or breastfeeding, ask a health professional before use. Keep out of reach children. In case of ingestion, get medical help or contact a Poison Control Center right away.

Directions

Clean affected area. Apply a small amount of this product on the area 1 to 3 times daily. Supervise children in the use of this product.

Keep out of reach of children

Other Information

°Store at controlled room temperature: 15-30°C (59-86F)

Tamper evident Feature: Do not use if cello-band cap is torn, broken or missing. Close tightly after use.

Inactive Ingredients:

Inactive Ingredients: Alcohol, Purified Water

Uses

Uses: First aid to help prevent infection in minor cuts, scrapes, and burns.

Violeta de Genciana

Violeta de Geniana

Gentian Violet

For External use only

Net Cont. 1 Fl. Oz (30mL)